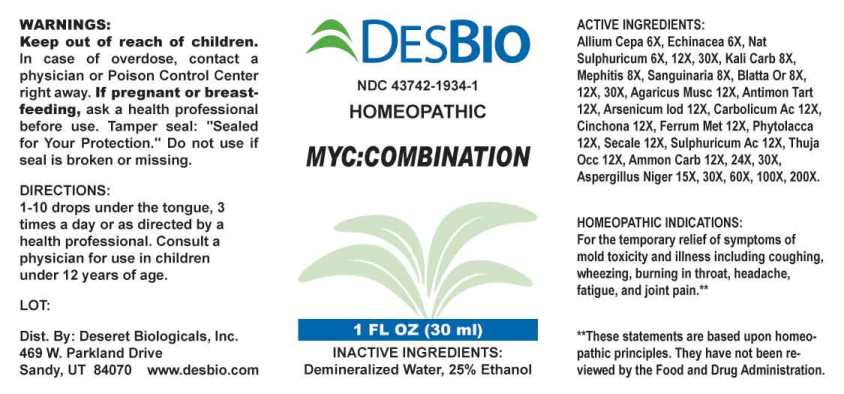 DRUG LABEL: MYCCombination
NDC: 43742-1934 | Form: LIQUID
Manufacturer: Deseret Biologicals, Inc.
Category: homeopathic | Type: HUMAN OTC DRUG LABEL
Date: 20231204

ACTIVE INGREDIENTS: ONION 6 [hp_X]/1 mL; ECHINACEA ANGUSTIFOLIA WHOLE 6 [hp_X]/1 mL; SODIUM SULFATE 6 [hp_X]/1 mL; POTASSIUM CARBONATE 8 [hp_X]/1 mL; MEPHITIS MEPHITIS ANAL GLAND FLUID 8 [hp_X]/1 mL; SANGUINARIA CANADENSIS ROOT 8 [hp_X]/1 mL; BLATTA ORIENTALIS 8 [hp_X]/1 mL; AMANITA MUSCARIA FRUITING BODY 12 [hp_X]/1 mL; ANTIMONY POTASSIUM TARTRATE 12 [hp_X]/1 mL; ARSENIC TRIIODIDE 12 [hp_X]/1 mL; PHENOL 12 [hp_X]/1 mL; CINCHONA OFFICINALIS BARK 12 [hp_X]/1 mL; IRON 12 [hp_X]/1 mL; PHYTOLACCA AMERICANA ROOT 12 [hp_X]/1 mL; CLAVICEPS PURPUREA SCLEROTIUM 12 [hp_X]/1 mL; SULFURIC ACID 12 [hp_X]/1 mL; THUJA OCCIDENTALIS LEAFY TWIG 12 [hp_X]/1 mL; AMMONIUM CARBONATE 12 [hp_X]/1 mL; ASPERGILLUS NIGER VAR. NIGER 15 [hp_X]/1 mL
INACTIVE INGREDIENTS: WATER; ALCOHOL

Drug Facts:

ACTIVE INGREDIENTS:

Allium Cepa 6X, Echinacea (Angustifolia) 6X, Natrum Sulphuricum 6X, 12X, 30X, Kali Carbonicum 8X, Mephitis Mephitica 8X, Sanguinaria Canadensis 8X, Blatta Orientalis 8X, 12X, 30X, Agaricus Muscarius 12X, Antimonium Tartaricum 12X, Arsenicum Iodatum 12X, Carbolicum Acidum 12X, Cinchona Officinalis 12X, Ferrum Metallicum 12X, Phytolacca Decandra 12X, Secale Cornutum 12X, Sulphuricum Acidum 12X, Thuja Occidentalis 12X, Ammonium Carbonicum 12X, 24X, 30X, Aspergillus Niger 15X, 30X, 60X, 100X, 200X.

HOMEOPATHIC INDICATIONS:

For the temporary relief of symptoms of mold toxicity and illness including coughing, wheezing, burning in throat, headache, fatigue, and joint pain.**

**These statements are based upon homeopathic principles. They have not been reviewed by the Food and Drug Administration.

WARNINGS:

Keep out of reach of children. In case of overdose, contact a physician or Poison Control Center right away.

If pregnant or breast-feeding, ask a health professional before use.

Tamper seal: "Sealed for Your Protection." Do not use if seal is broken or missing.

Keep out of reach of children. In case of overdose, contact a physician or Poison Control Center right away.

DIRECTIONS:

1-10 drops under the tongue, 3 times a day or as directed by a health professional. Consult a physician for use in children under 12 years of age.

HOMEOPATHIC INDICATIONS:

For the temporary relief of symptoms of mold toxicity and illness including coughing, wheezing, burning in throat, headache, fatigue, and joint pain.**

**These statements are based upon homeopathic principles. They have not been reviewed by the Food and Drug Administration.

INACTIVE INGREDIENTS:

Demineralized Water, 25% Ethanol

QUESTIONS:

Dist. By: Deseret Biologicals, Inc.

469 W. Parkland Drive

Sandy, UT 84070 www.desbio.com

PACKAGE LABEL DISPLAY:

DESBIO
NDC 43742-1934-1
HOMEOPATHIC
MYC:Combination
1 FL OZ (30 ml)